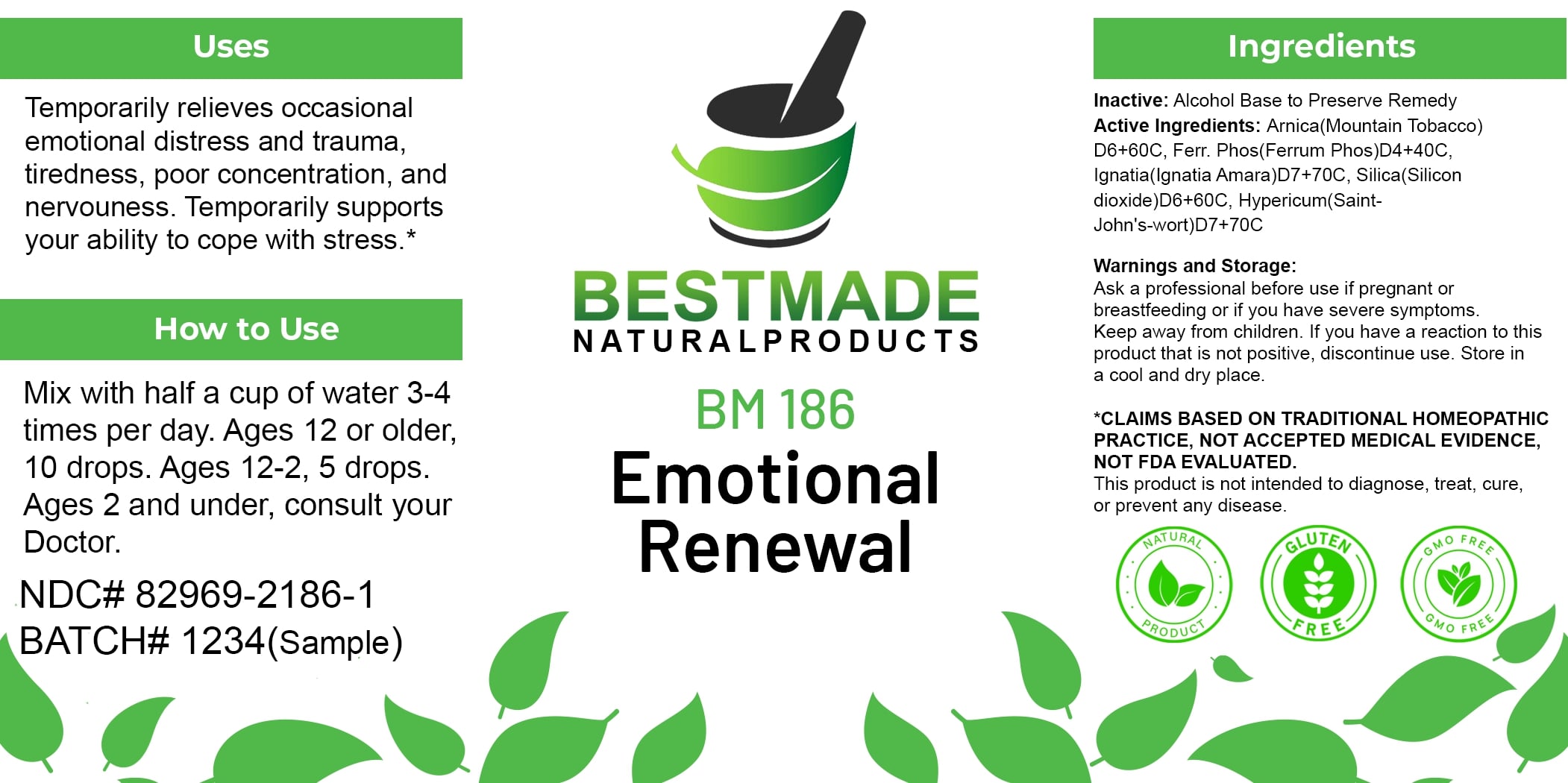 DRUG LABEL: Bestmade Natural Products BM186
NDC: 82969-2186 | Form: LIQUID
Manufacturer: Bestmade Natural Products
Category: homeopathic | Type: HUMAN OTC DRUG LABEL
Date: 20250220

ACTIVE INGREDIENTS: FERROSOFERRIC PHOSPHATE 30 [hp_C]/30 [hp_C]; ARNICA MONTANA 30 [hp_C]/30 [hp_C]; STRYCHNOS IGNATII SEED 30 [hp_C]/30 [hp_C]; HYPERICUM PERFORATUM 30 [hp_C]/30 [hp_C]; SILICA 30 [hp_C]/30 [hp_C]
INACTIVE INGREDIENTS: ALCOHOL 30 [hp_C]/30 [hp_C]

BM186

DOSAGE AND ADMINISTRATION

How to Use

Mix with half a cup of water 3-4 times per day. Ages 12 or older, 10 drops. Ages 12-2, 5 drops. Ages 2 and under, consult your Doctor.

Uses

Temporarily relieves occasional emotional distress and trauma, tiredness, poor concentration, and nervousness. Temporarily supports your ability to cope with stress.*

*CLAIMS BASED ON TRADITIONAL HOMEOPATHIC PRACTICE, NOT ACCEPTED MEDICAL EVIDENCE. NOT FDA EVALUATED.

This product is not intended to diagnose, treat, cure, or prevent any disease.

INACTIVE INGREDIENT

Ingredients

Inactive: Alcohol Base to Preserve Remedy

ACTIVE INGREDIENT

Active Ingredients: Arnica(Mountain Tobacco) D6+60C, Ferr Phos(Ferrum Phos)D4+40C, Ignatia(Ignatia Amara)D7+70C, Silica(Silicon dioxide)D6+60C, Hypericum(Saint-John's-wort)D7+70C

KEEP OUT OF REACH OF CHILDREN

Warnings and Storage:

Ask a professional before use if pregnant or breastfeeding or if you have severe symptoms. Keep away from children. If you have a reaction to this product that is not positive, discontinue use. Store in a cool and dry place.

Warnings and Storage:

Ask a professional before use if pregnant or breastfeeding or if you have severe symptoms. Keep away from children. If you have a reaction to this product that is not positive, discontinue use. Store in a cool and dry place.

*CLAIMS BASED ON TRADITIONAL HOMEOPATHIC PRACTICE, NOT ACCEPTED MEDICAL EVIDENCE. NOT FDA EVALUATED.

This product is not intended to diagnose, treat, cure, or prevent any disease.

Uses

Temporarily relieves occasional emotional distress and trauma, tiredness, poor concentration, and nervousness. Temporarily supports your ability to cope with stress.*

*CLAIMS BASED ON TRADITIONAL HOMEOPATHIC PRACTICE, NOT ACCEPTED MEDICAL EVIDENCE. NOT FDA EVALUATED.

This product is not intended to diagnose, treat, cure, or prevent any disease.

Entire package label